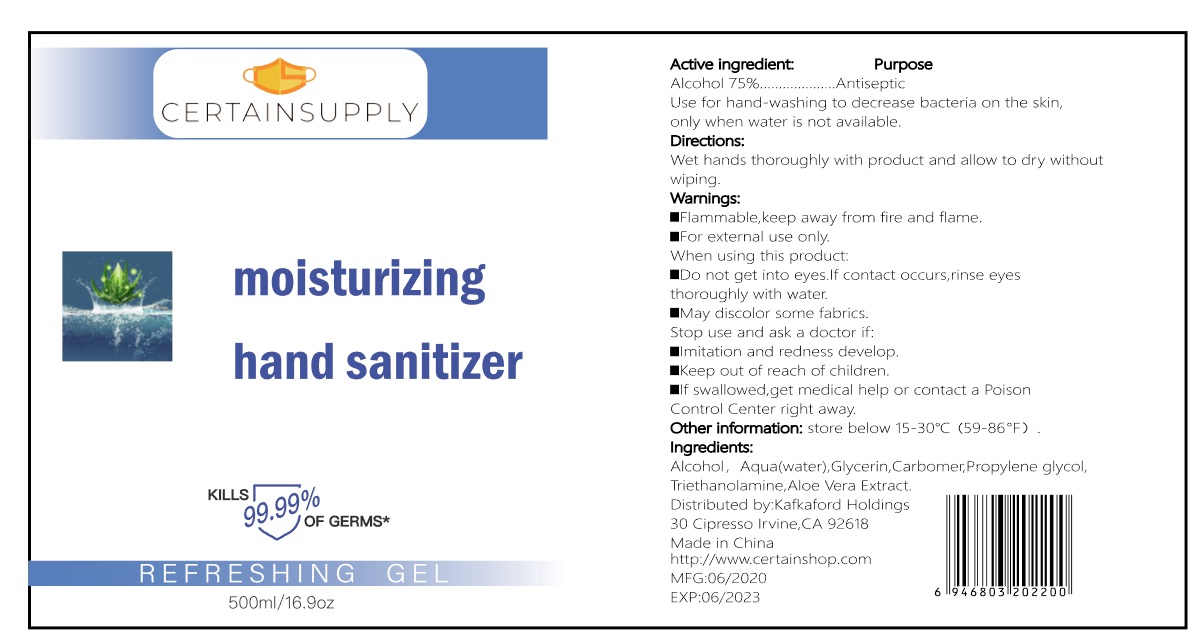 DRUG LABEL: CERTAINSUPPLY Moisturizing Hand Sanitizer
NDC: 77975-008 | Form: GEL
Manufacturer: Guangzhou Tingcai Cosmetic Co., Ltd.
Category: otc | Type: HUMAN OTC DRUG LABEL
Date: 20200709

ACTIVE INGREDIENTS: ALCOHOL 75 mL/100 mL
INACTIVE INGREDIENTS: WATER; GLYCERIN; PROPYLENE GLYCOL; TROLAMINE

HAND SANITIZER

Active ingredient

Alcohol ............. 75%

Purpose

Antiseptic

Use

Use for hand-washing to Decreases bacteria on skin, when water is not available.

Warnings

For external use only.

Flammable. Keep product away from fire or flame.

When using this product Do not get into eyes. If contact occurs, rinse eyes thoroughly with water.

Stop use and ask a doctor if redness or irritation develop.

Other information:

Store below 15-30 ℃ (59-86 ℉)

Keep out of reach of children.

If swallowed, get medical help or contact a Poison Control Center right away.

Directions

Wet hands thoroughly with product and allow to dry without wiping.

Inactive ingredients

Water (Aqua), Glycerin, Carbomer, Propylene glycol, Triethanolamine, Aloe Vera Extract.